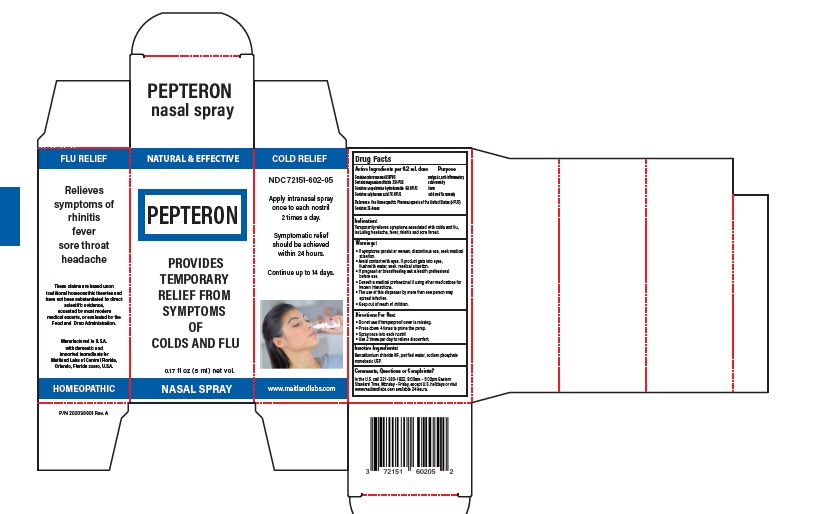 DRUG LABEL: PEPTERON
NDC: 72151-602 | Form: SPRAY, METERED
Manufacturer: Maitland Labs of Central Florida
Category: homeopathic | Type: HUMAN OTC DRUG LABEL
Date: 20200326

ACTIVE INGREDIENTS: NAJA NAJA WHOLE 4 [hp_X]/0.2 mL; MAGNESIUM CHLORIDE 2 [hp_X]/0.2 mL; SCOPOLAMINE HYDROBROMIDE 6 [hp_X]/0.2 mL; SULFUROUS ACID 7 [hp_X]/0.2 mL
INACTIVE INGREDIENTS: BENZALKONIUM CHLORIDE; WATER; SODIUM PHOSPHATE, MONOBASIC, ANHYDROUS

PEPTERON

Active Ingredients per dose Purpose

Contains cobra venom 4X HPUS analgesic, anti-inflammatory
Contains magnesium chloride 2X HPUS cold remedy

Contains scopolamine hydrobromide 6X HPUS fever

Contains sulphurous acid 7X HPUS cold and flu remedy

Reference :the Homeopathic Pharmacopoeia of the United States (HPUS)

Contains 25 doses

Warning

- If symptoms persist or worsen, discontinue use, seek medical attention
- Avoid contact with eyes. If product gets into eyes,flush with water, seek medical attention
- If pregnant or breastfeeding ask a health professional before use
- Consult a medical professional if using other medications for known interactions
- The use of this dispenser by more than one person may spread infection.
- keep out of reach of children.

Purpose

Temporarily relieves symptoms associated with colds and flu,including headache, fever, rhinitis and sore throat.

Indication

Temporarily relieves symptoms associated with colds and flu,including headache, fever, rhinitis and sore throat.

Directions For Use

• Do not use if tamperproof cover is missing

• Press down 4 times to prime the pump.

- spray once in to each nostril.
- Use 2 times per day to relieve discomfort.

Keep out of reach of childrens.

Comments, Questions or Complaints?

In the U.S. call 321-280-1922, 9:00am - 5:00pm Eastern

Standard Time, Monday - Friday, except U.S. holidays or visit

www.maitlandlabs.com available 24 hours.

Inactive ingredient section

Benzalkonium chloride NF, purified water, sodium phosphate,monobasics USP